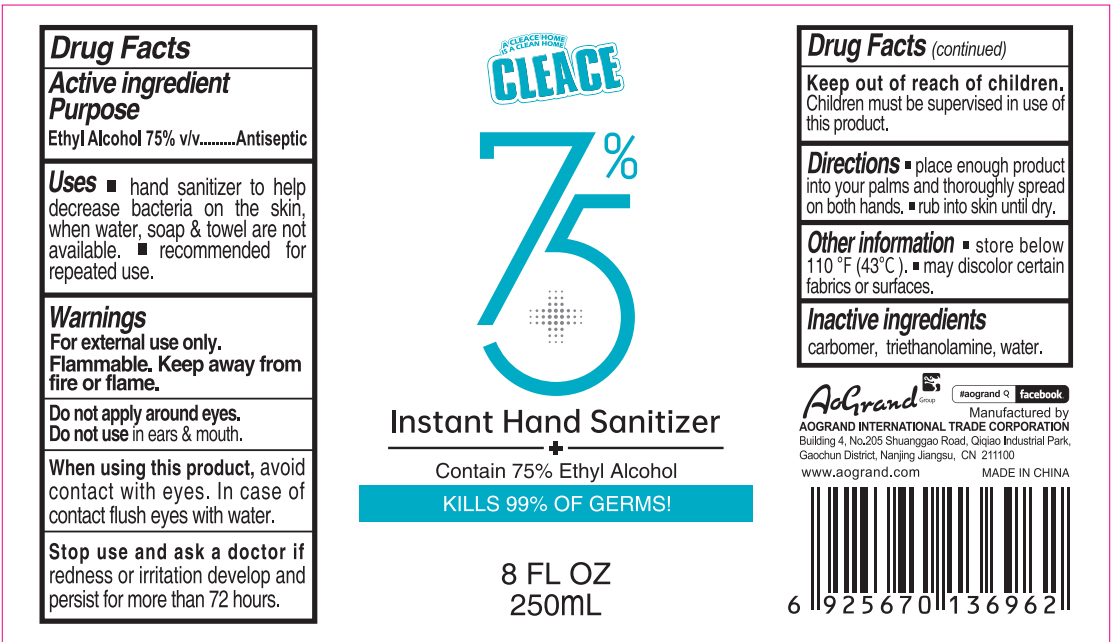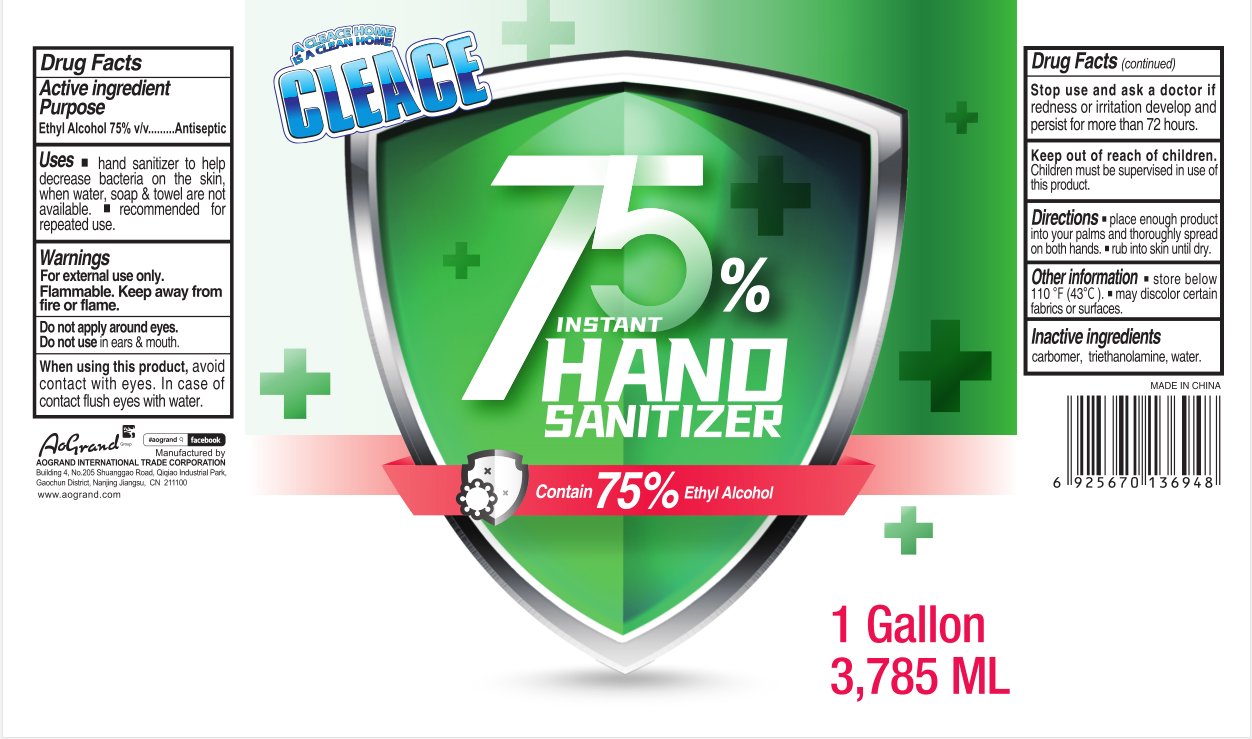 DRUG LABEL: CLEACE 75% Alcohol hand sanitizer
NDC: 74621-013 | Form: GEL
Manufacturer: Aogrand International Trade Corporation
Category: otc | Type: HUMAN OTC DRUG LABEL
Date: 20230211

ACTIVE INGREDIENTS: ALCOHOL 75 mL/100 mL
INACTIVE INGREDIENTS: CARBOMER HOMOPOLYMER, UNSPECIFIED TYPE; WATER; TROLAMINE

CLEACE 75% Alcohol hand sanitizer

Active Ingredient

Alcohol 75% v/v. Purpose: Antiseptic

Purpose

Antiseptic, Hand Sanitizer

Uses

- hand sanitizer to help decrease bacteria on the skin, when water, soap & towel are not available.
- recommended for repeated use.

Warnings

For external use only.

Flammable. Keep away from fire or flame.

Do not apply around eyes.

Do not use in ears & mouth.

When using this product

avoid contact with eyes. In case of cntact flush eyes with water.

Stop use and ask a doctor if

redness or irritation develop and persist for more than 72 hours

Keep out of reach of children.

Children must be supervised in use of this product.

Directions

- place enough product into your palms and thoroughly spread on both hands.
- rub into skin until dry.

Other information

- store below 110F (43C)
- may discolor certain fabrics or surfaces.

Inactive ingredients

carbomer, triethanolamine, water

Package Label - Principal Display Panel

250 mL NDC: 74621-013-01

A CLEACE HOME

IS A CLEAN HOME

CLEACE

75% Instant Hand Sanitizer

+

Contain 75% Ethyl Alcohol

KILLS 99% OF GERMS!

8 FL OZ

250mL

3785 mL NDC: 74621-013-02

A CLEACE HOME

IS A CLEAN HOME

CLEACE

75% Instant Hand Sanitizer

Contain 75% Ethyl Alcohol

1 Gallon

3,785mL